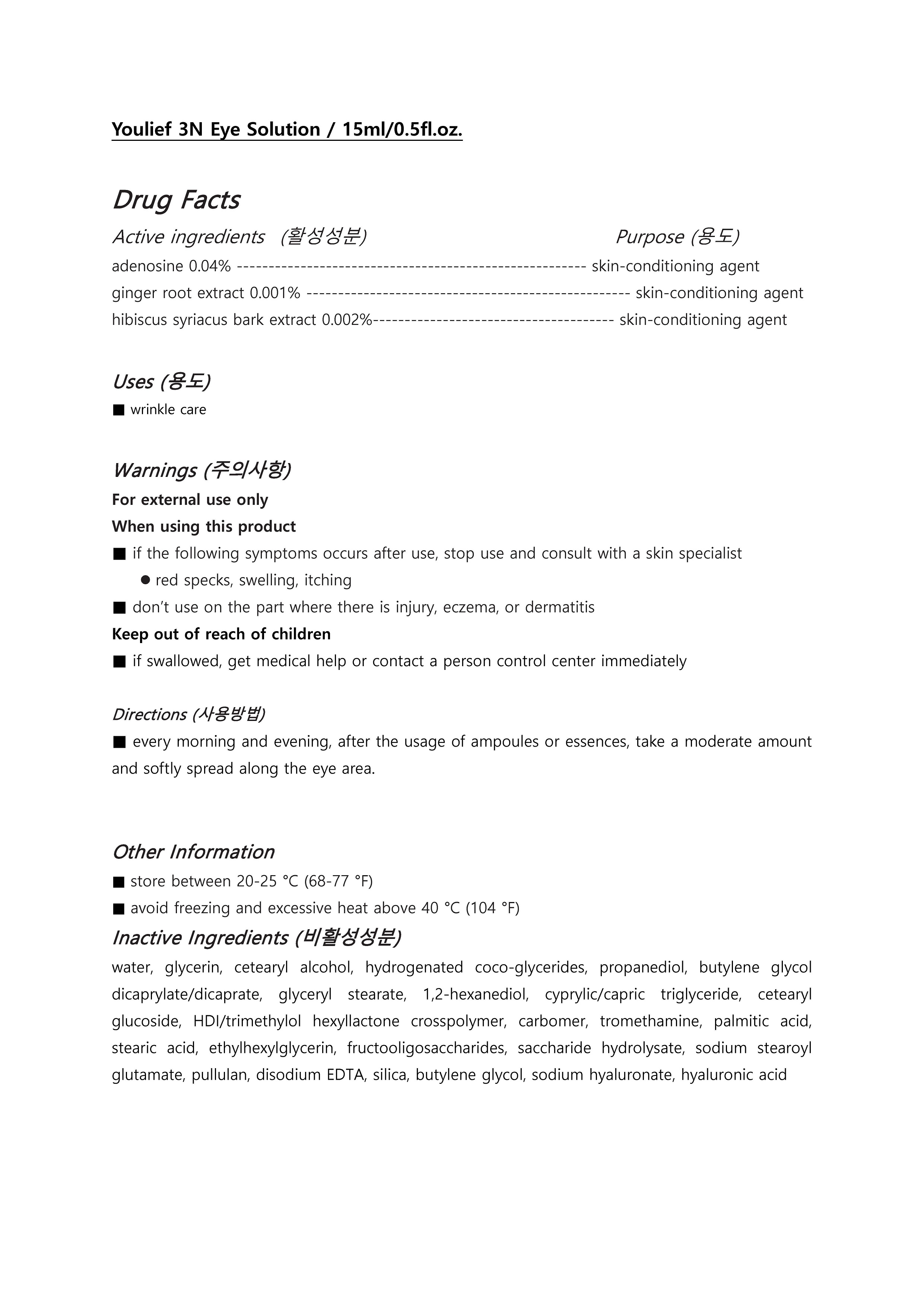 DRUG LABEL: Youlief 3N EyeSolution
NDC: 73560-0002 | Form: SOLUTION
Manufacturer: Plcoskin
Category: otc | Type: HUMAN OTC DRUG LABEL
Date: 20200127

ACTIVE INGREDIENTS: HIBISCUS SYRIACUS BARK 0.002 g/100 mL; ADENOSINE 0.04 g/100 mL; GINGER 0.001 g/100 mL
INACTIVE INGREDIENTS: WATER; BUTYLENE GLYCOL

Drug Facts

ACTIVE INGREDIENT

Adenosine, ginger root extract, hibiscus syriacus bark extract

INACTIVE INGREDIENT

WATER, BUTYLENE GLYCOL, GLYCERIN,
PROPANEDIOL, DIGLYCERIN,
1,2-HEXANEDIOL, GLYCERETH-25
PCA ISOSTEARATE, CAFFEINE,
HYDROXYETHYLCELLULOSE, CAPRYLYL
GLYCOL, CARBOMER, TROMETHAMINE,
ETHYLHEXYLGLYCERIN, *ADENOSINE,
ACETYL GLUCOSAMINE, DISODIUM EDTA,
SODIUM HYALURONATE, BETA-GLUCAN,
HYDROLYZED SODIUM HYALURONATE,
HYDROLYZED HYALURONIC ACID,
*LOTUS JAPONICUS SOMATIC EMBRYO
EXTRACT, HYDROXYPROPYLTRIMONIUM
HYALURONATE, *ZINGIBER OFFICINALE
(GINGER) ROOT EXTRACT

PURPOSE

anti-wrinkle

keep out of reach of the children

INDICATIONS AND USAGE

Every morning and evening, after the usage of ampoules or essences, take a moderate amount of the cosmetics and softly spread along the eye area and parts where wrinkles are considerates then gently pat for the skin to absorb.

WARNINGS

For external use only
When using this product

■ if the following symptoms occurs after use, stop use and consult with a skin specialist

red specks, swelling, itching

■ don’t use on the part where there is injury, eczema, or dermatitis

Keep out of reach of children

■ if swallowed, get medical help or contact a person control center immediately

DOSAGE AND ADMINISTRATION

for external use only